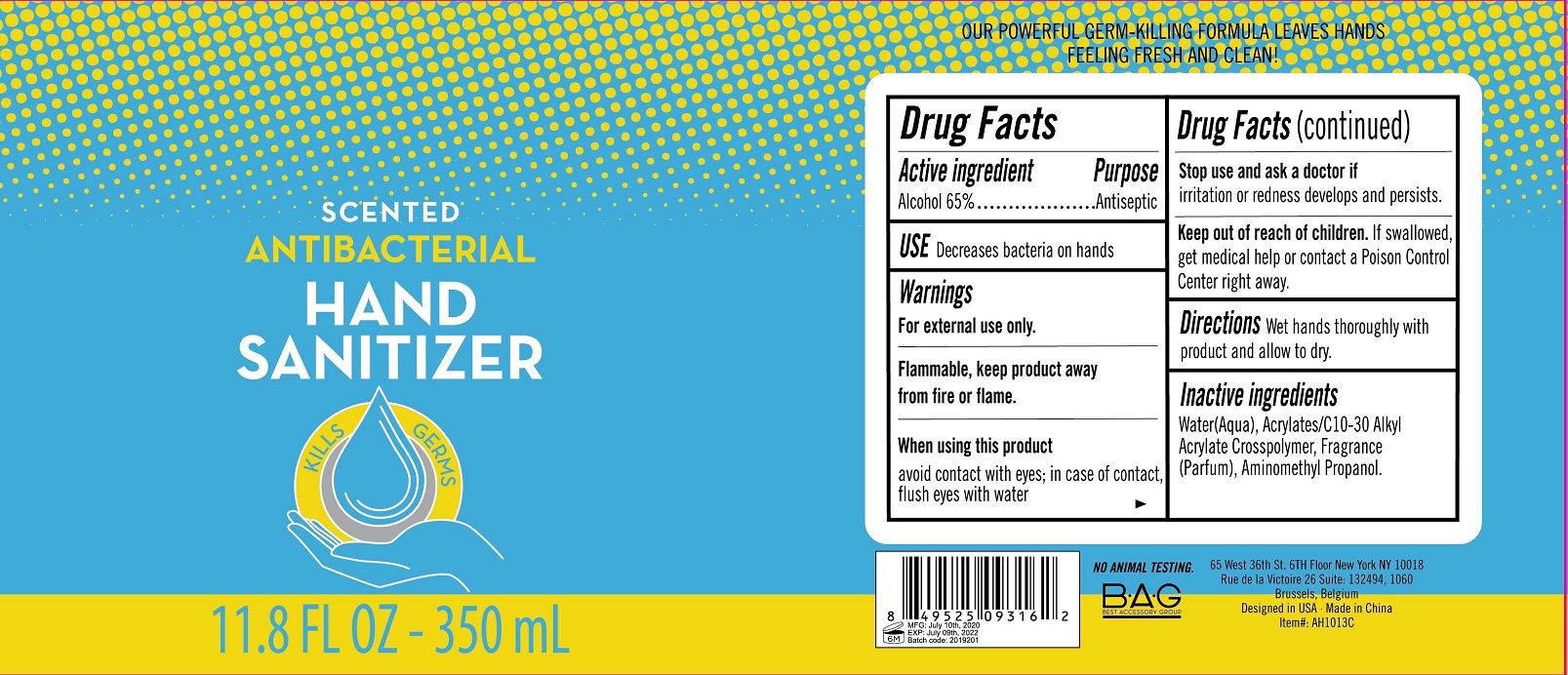 DRUG LABEL: scented antibacterial hand sanitizer
NDC: 56136-370 | Form: GEL
Manufacturer: Ganzhou Olivee Cosmetic Co., Ltd.
Category: otc | Type: HUMAN OTC DRUG LABEL
Date: 20200713

ACTIVE INGREDIENTS: ALCOHOL 65 mL/100 mL
INACTIVE INGREDIENTS: WATER; CARBOMER COPOLYMER TYPE A; AMINOMETHYLPROPANOL

HAND SANITIZER

Active ingredient

Alcohol ............. 65%

Purpose

Antiseptic

Use

Decreases bacteria on skin

Warnings

For external use only.

Flammable. Keep product away from fire or flame.

When using this product avoid contact with eyes. In case of contact, flush eyes with water.

Stop use and ask a doctor if redness or irritation develops and persists.

Keep out of reach of children.

If swallowed, get medical help or contact a Poison Control Center right away.

Directions

Wet hands thoroughly with product and allow to dry

Inactive ingredients

Water (Aqua), Acrylates/C10-30 Alkyl Acrylate Crosspolymer, Aminomethyl Propanol, Fragrance (Parfum)